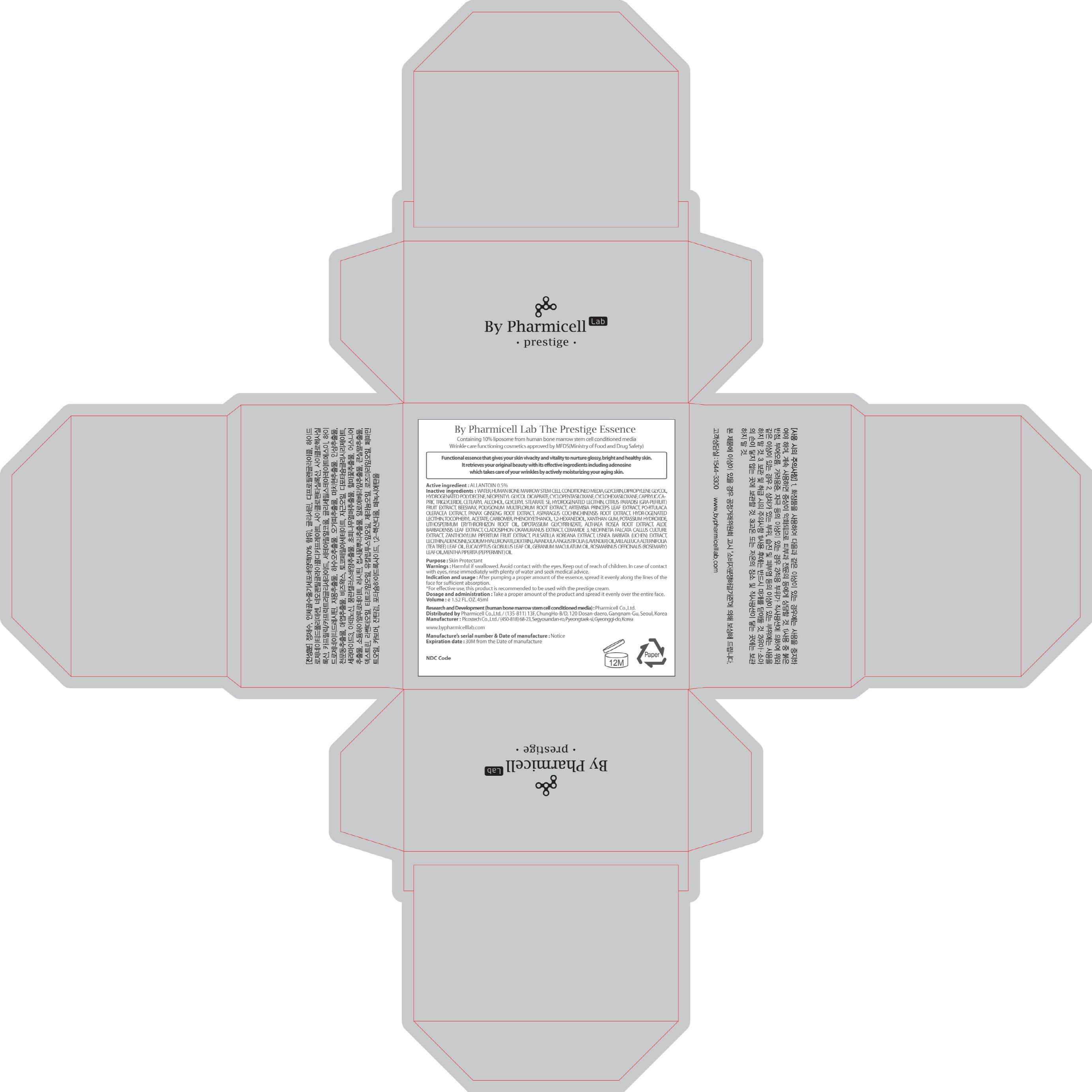 DRUG LABEL: The Prestige Essence
NDC: 60949-170 | Form: CREAM
Manufacturer: Pharmicell Co., Ltd.
Category: otc | Type: HUMAN OTC DRUG LABEL
Date: 20140922

ACTIVE INGREDIENTS: ALLANTOIN 0.22 mg/45 mL
INACTIVE INGREDIENTS: WATER; GLYCERIN

ACTIVE INGREDIENT

Active ingredient : ALLANTOIN 0.5%

INACTIVE INGREDIENT

Inactive ingredients : WATER, HUMAN BONE MARROW STEM CELL CONDITIONED MEDIA, GLYCERIN, DIPROPYLENE GLYCOL, HYDROGENATED POLYDECENE, NEOPENTYL GLYCOL DICAPRATE, CYCLOPENTASILOXANE, CYCLOHEXASILOXANE, CAPRYLIC/CAPRIC TRIGLYCERIDE, CETEARYL ALCOHOL, GLYCERYL STEARATE SE, HYDROGENATED LECITHIN, CITRUS PARADISI (GRAPEFRUIT) FRUIT EXTRACT, BEESWAX, POLYGONUM MULTIFLORUM ROOT EXTRACT, ARTEMISIA PRINCEPS LEAF EXTRACT, PORTULACA OLERACEA EXTRACT, PANAX GINSENG ROOT EXTRACT, ASPARAGUS COCHINCHINENSIS ROOT EXTRACT, HYDROGENATED LECITHIN, TOCOPHERYL ACETATE, CARBOMER, PHENOXYETHANOL, 1,2-HEXANEDIOL, XANTHAN GUM, POTASSIUM HYDROXIDE, LITHOSPERMUM ERYTHRORHIZON ROOT OIL, DIPOTASSIUM GLYCYRRHIZATE, ALTHAEA ROSEA ROOT EXTRACT, ALOE BARBADENSIS LEAF EXTRACT, CLADOSIPHON OKAMURANUS EXTRACT, CERAMIDE 3, NEOFINETIA FALCATA CALLUS CULTURE EXTRACT, ZANTHOXYLUM PIPERITUM FRUIT EXTRACT, PULSATILLA KOREANA EXTRACT, USNEA BARBATA (LICHEN) EXTRACT, LECITHIN, ADENOSINE, SODIUM HYALURONATE, DEXTRIN, LAVANDULA ANGUSTIFOLIA (LAVENDER) OIL, MELALEUCA ALTERNIFOLIA (TEA TREE) LEAF OIL, EUCALYPTUS GLOBULUS LEAF OIL, GERANIUM MACULATUM OIL, ROSMARINUS OFFICINALIS (ROSEMARY) LEAF OIL, MENTHA PIPERITA (PEPPERMINT) OIL

PURPOSE

Purpose : Skin Protectant

WARNINGS

Warnings : Harmful if swallowed. Avoid contact with the eyes. Keep out of reach of children. In case of contact with eyes, rinse immediately with plenty of water and seek medical advice.

INDICATIONS & USAGE

Indication and usage : After pumping a proper amount of the essence, spread it evenly along the lines of the face for sufficient absorption.
-For effective use, this product is recommended to be used with the prestige cream.

DOSAGE & ADMINISTRATION

Dosage and administration : Take a proper amount of the product and spread it evenly over the entire face.

KEEP OUT OF REACH OF CHILDREN